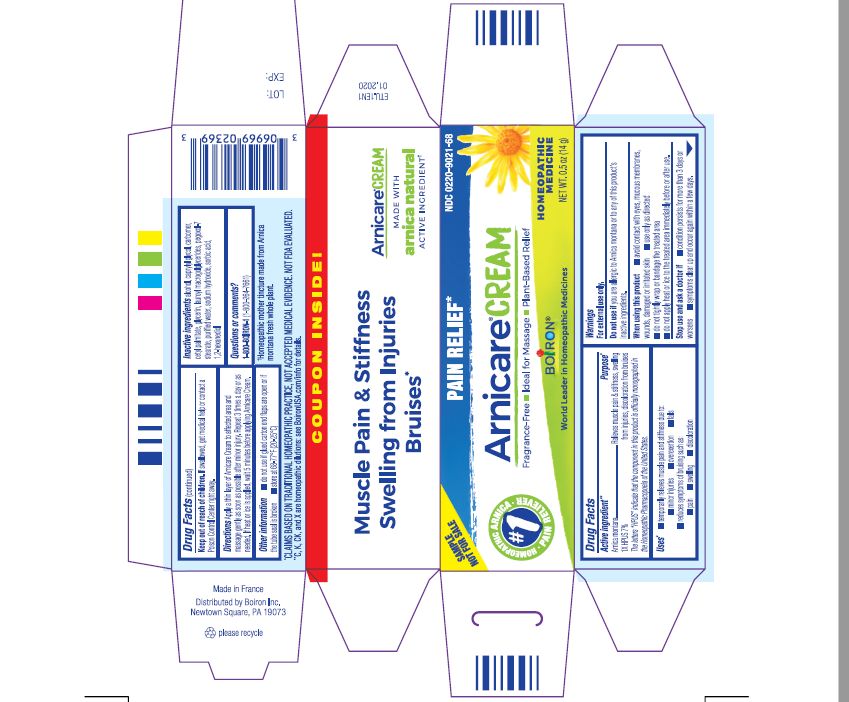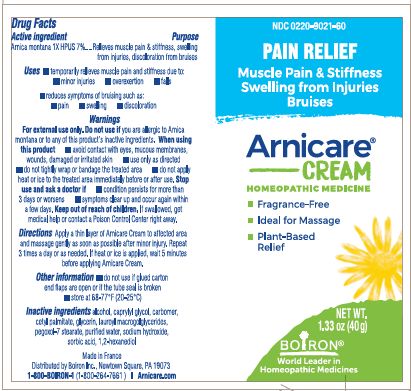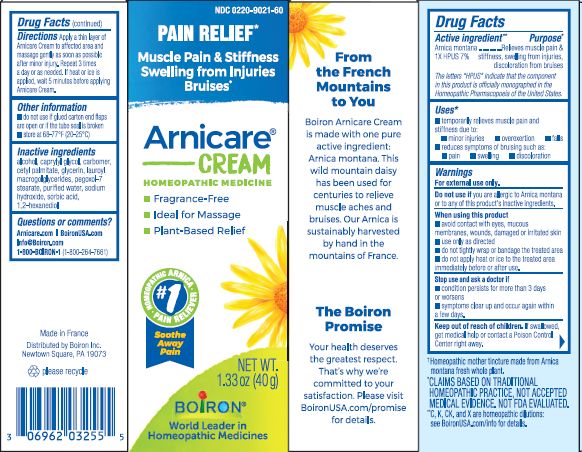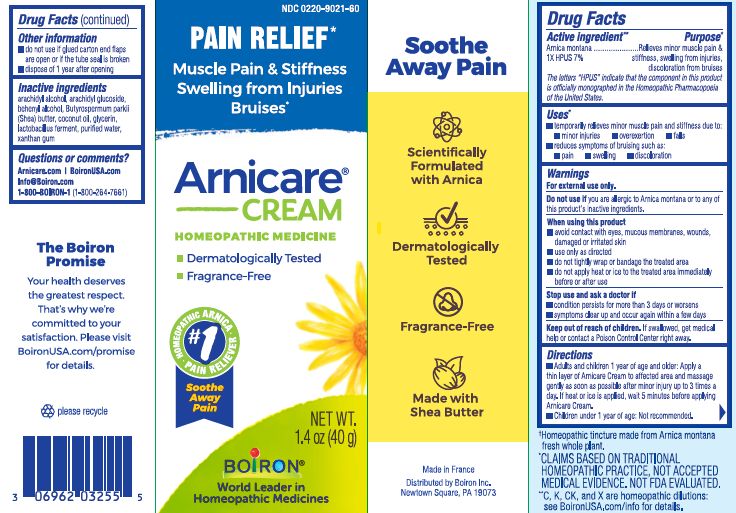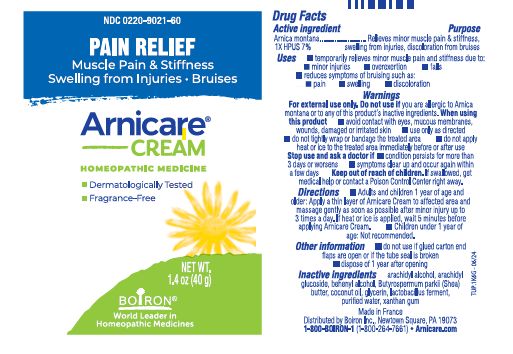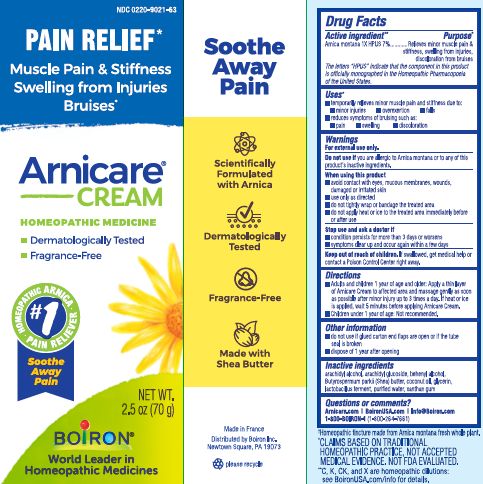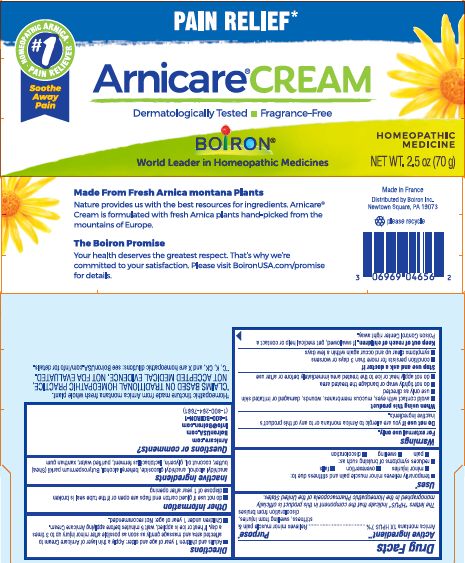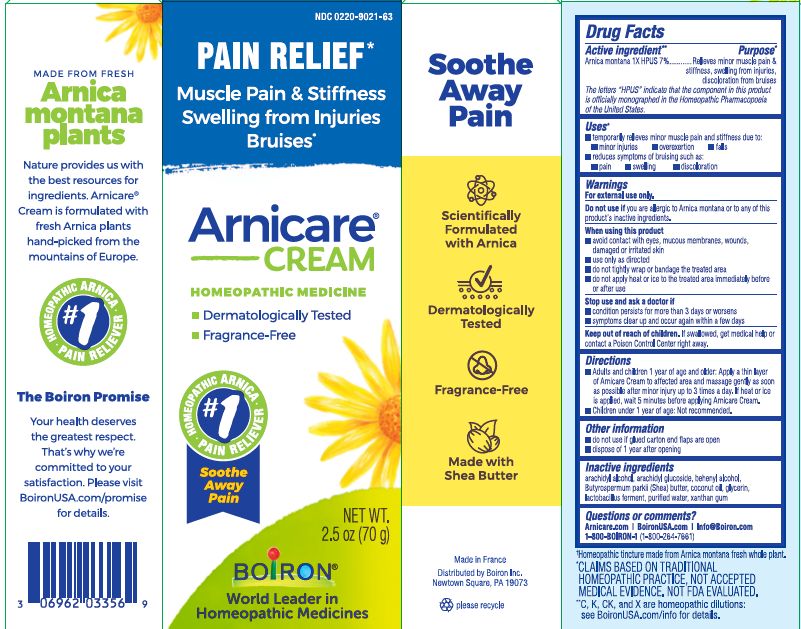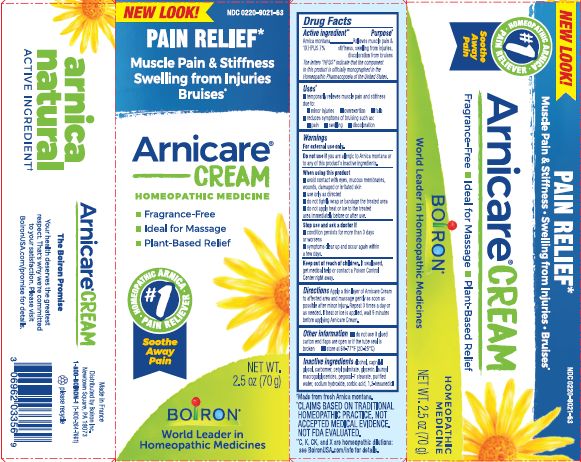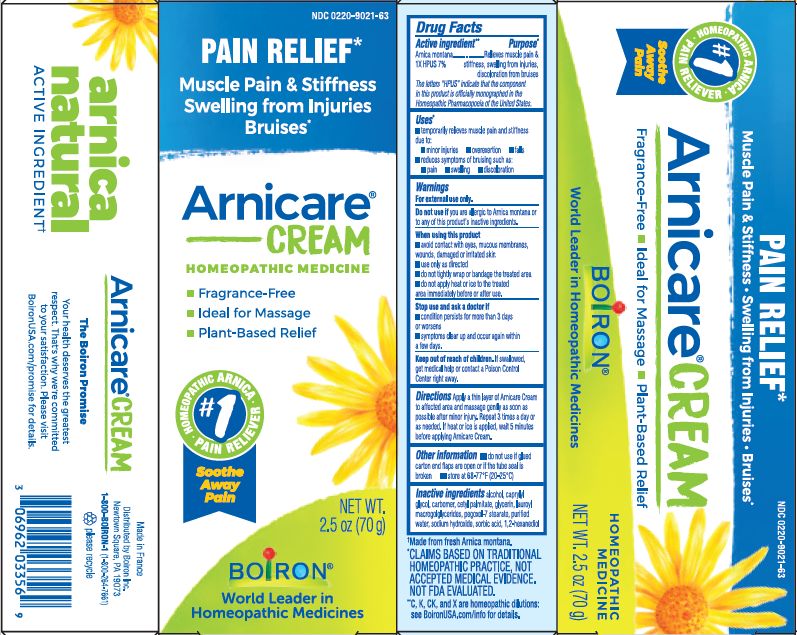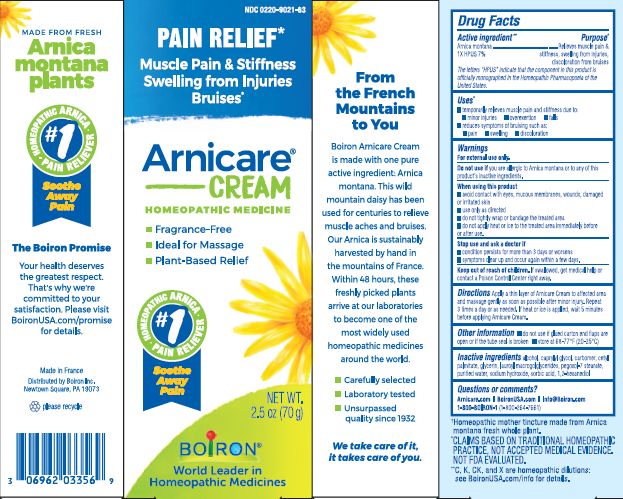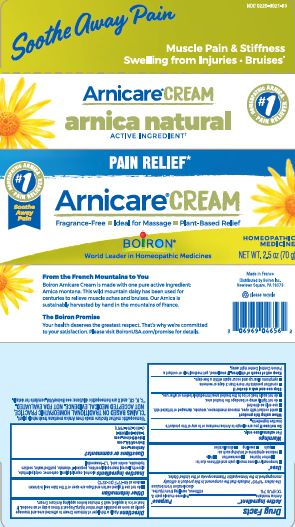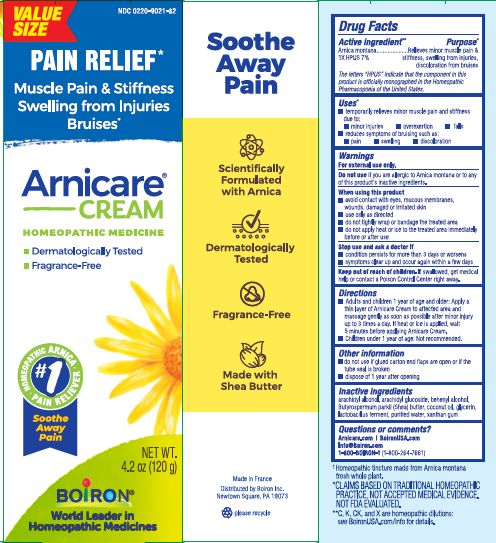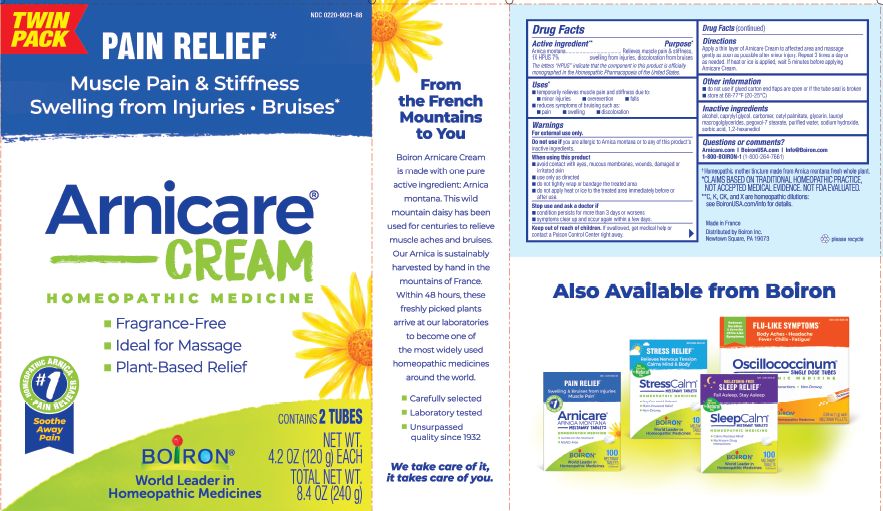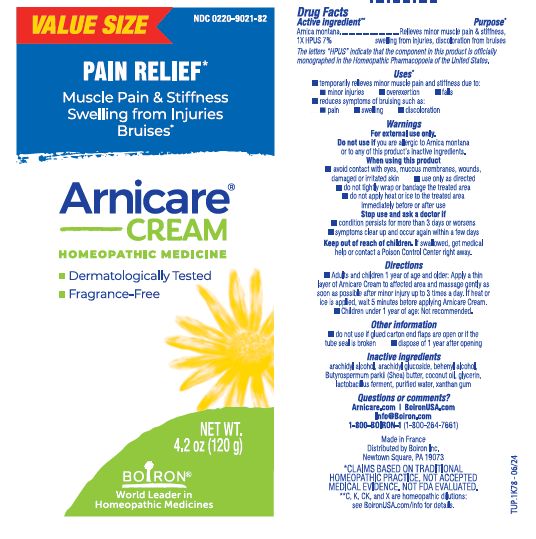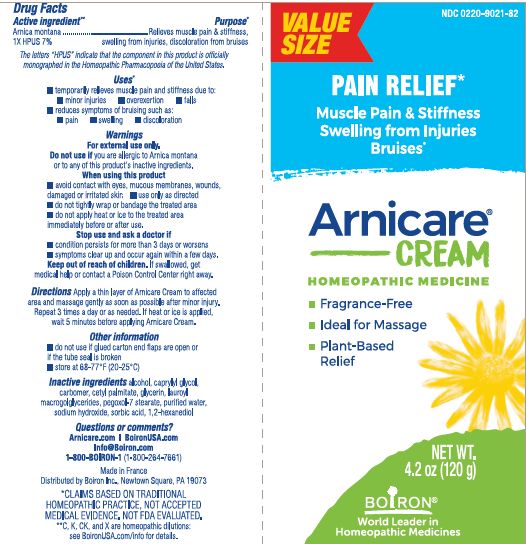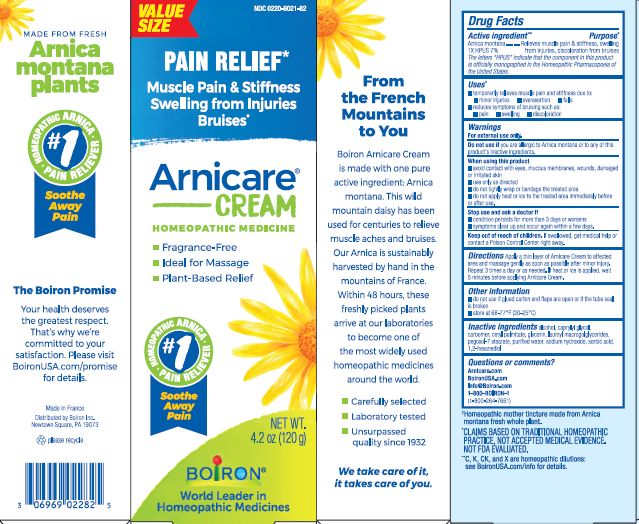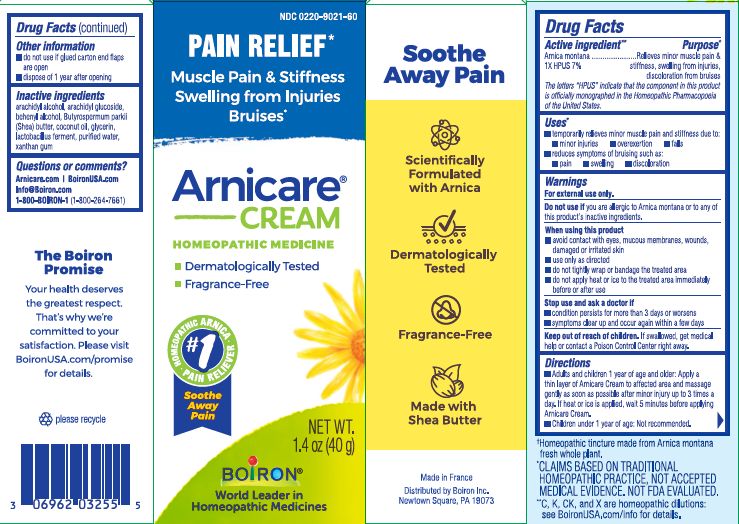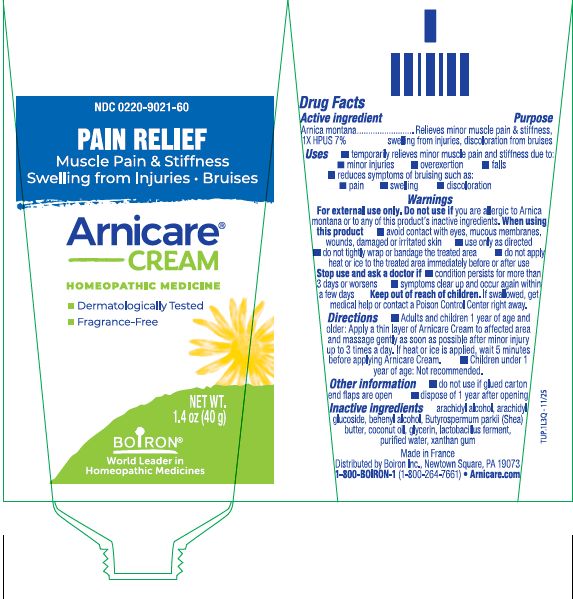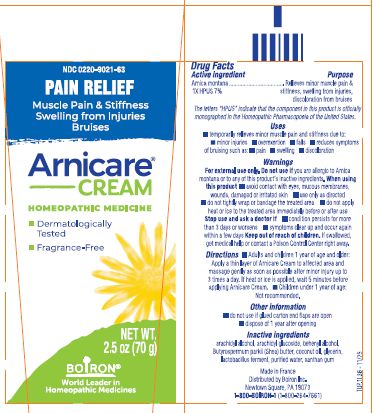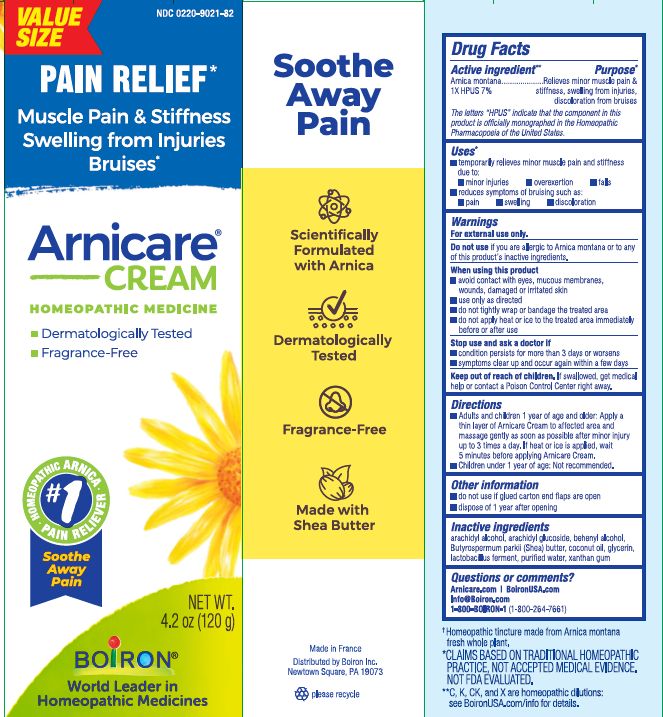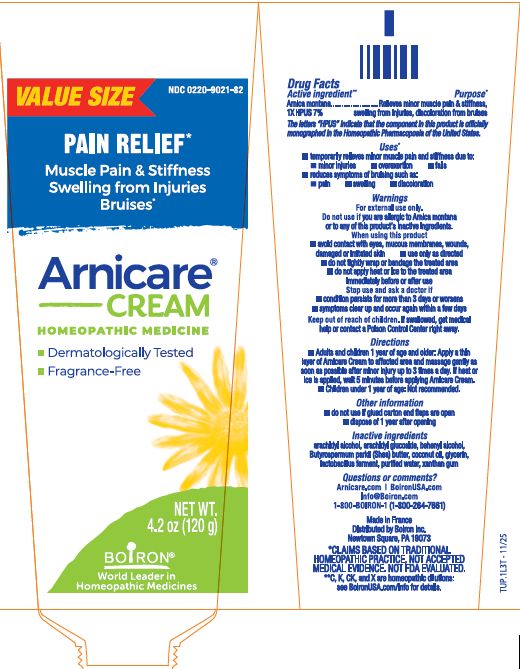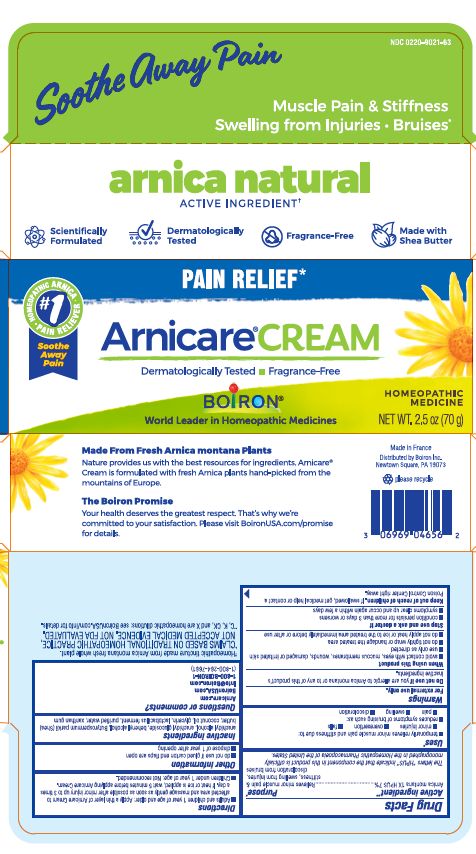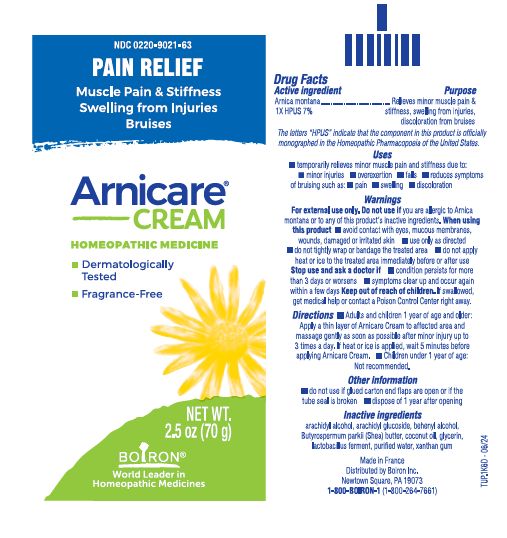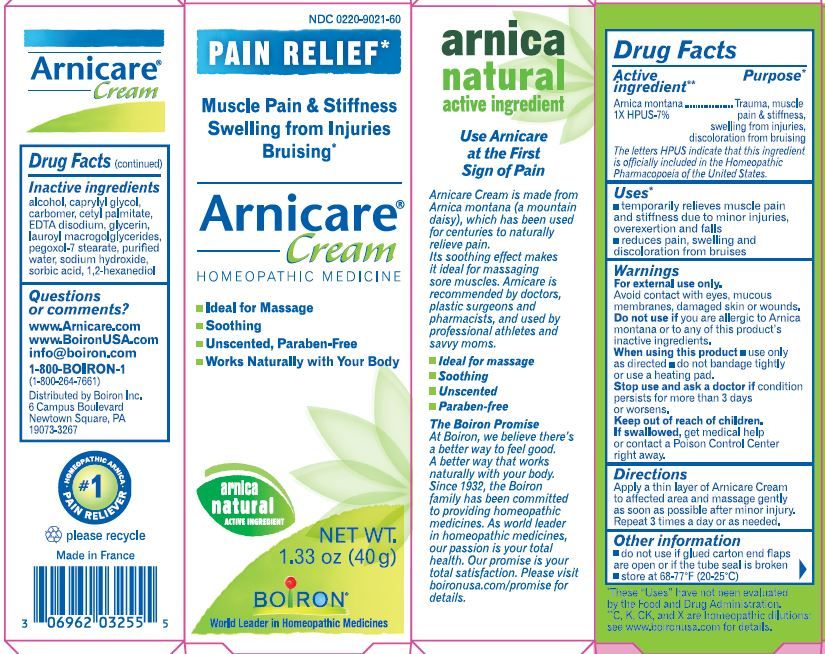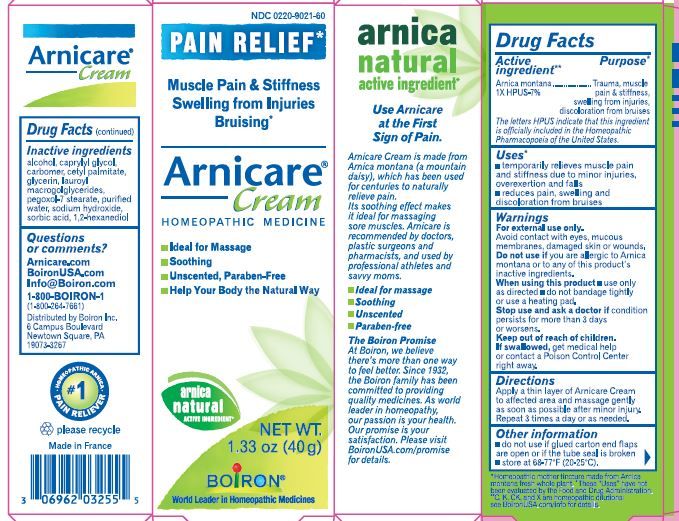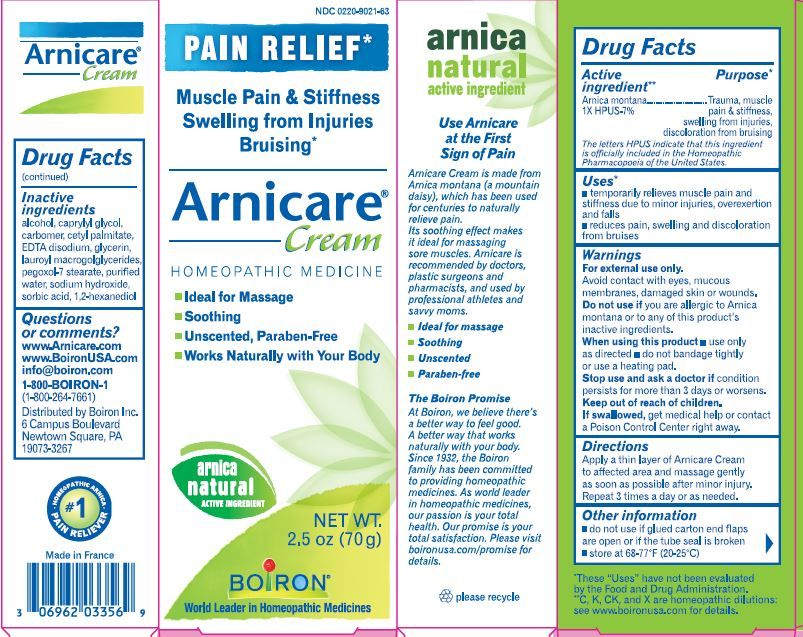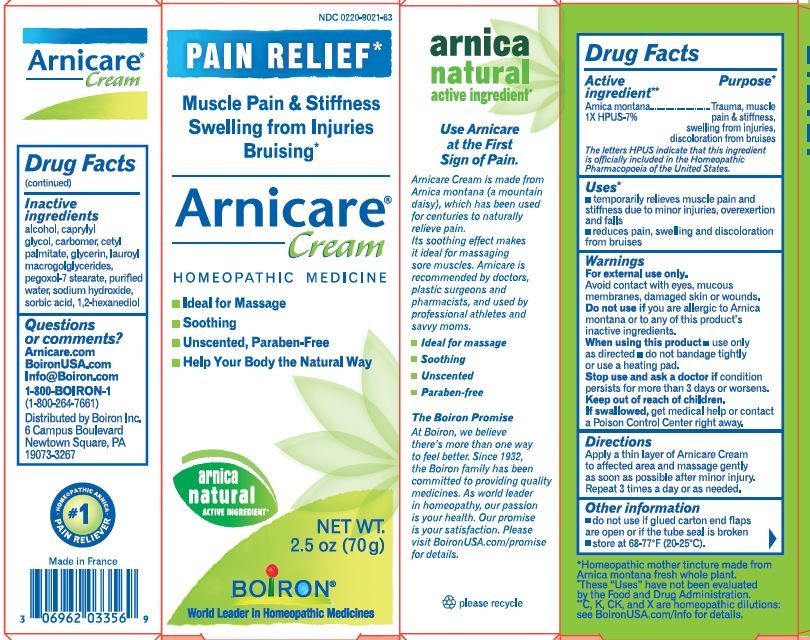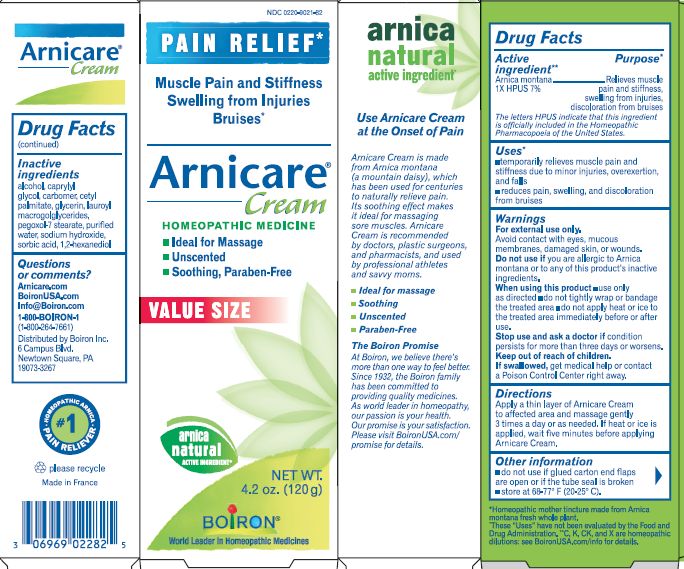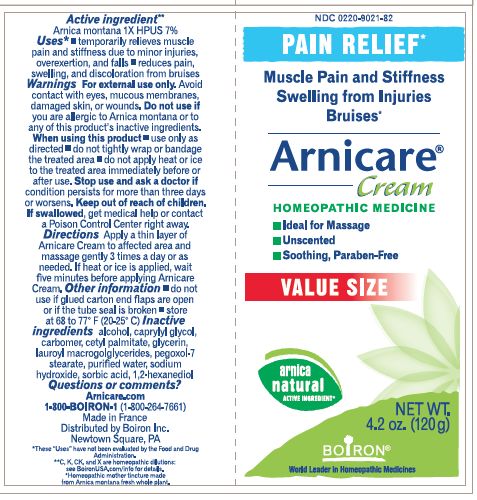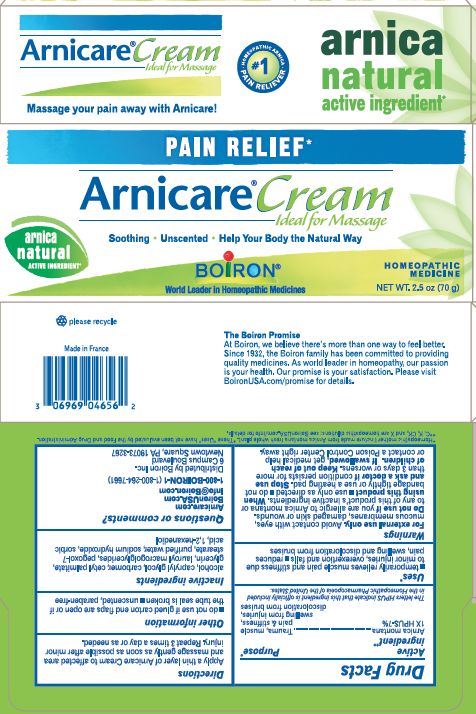 DRUG LABEL: ARNICARE
NDC: 0220-9021 | Form: CREAM
Manufacturer: Laboratoires Boiron
Category: homeopathic | Type: HUMAN OTC DRUG LABEL
Date: 20251212

ACTIVE INGREDIENTS: ARNICA MONTANA 1 [hp_X]/1 g
INACTIVE INGREDIENTS: ARACHIDYL GLUCOSIDE; GLYCERIN; DOCOSANOL; WATER; COCONUT OIL; ARACHIDYL ALCOHOL; XANTHAN GUM; LIMOSILACTOBACILLUS FERMENTUM; BUTYROSPERMUM PARKII (SHEA) BUTTER UNSAPONIFIABLES

Arnicare Cream

Active ingredient**

Arnica montana 1X HPUS 7%

The letters "HPUS" indicate that the component in this product are officially monographed in the Homeopathic Pharmacopoeia of the United States.

Purpose*

Relieves minor muscle pain & stiffness, swelling from injuries, discoloration from bruises

INDICATIONS AND USAGE

- temporarily relieves minor muscle pain and stiffness due to:
- minor injuries
- overexertion
- falls
- reduces symptoms of bruising such as:
- pain
- swelling
- discoloration

WARNINGS

For external use only.

Do not use if you are allergic to Arnica montana or to any of this product's inactive ingredients.

When using this product

- avoid contact with eyes, mucous membranes, wounds, damaged or irritated skin
- use only as directed
- do not tightly wrap or bandage the treated area
- do not apply heat or ice to threated area immediately before or after use

Stop use and ask a doctor if

- condition persists for more than 3 days or worsens
- symptoms clear up and occur again within a few days

Keep out of reach of children. If swallowed, get medical help or contact a Poison Control Center right away.

DOSAGE AND ADMINISTRATION

- Adults and children 1 year of age and older: Apply a thin layer of Arnicare cream to affected area and massage gently as soon as possible after minor injury up to 3 times a day. If heat or ice is applied, wait 5 minutes before applying Arnicare Cream.
- Children under 1 year of age: Not recommended.

INACTIVE INGREDIENT

arachidyl alcohol, arachidyl glucoside, behenyl alcohol, Butyrospermum parkii (Shea) butter, coconut oil, glycerin, lactobacillus ferment, purified water, xanthan gum

alcohol, caprylyl glycol, carbomer, cetyl palmitate, glycerin, lauroyl, macrogolglycerides, pegoxol-7 stearate, purified water, sodium hydroxide, sorbic acid, 1,2-hexanediol

QUESTIONS

Arnicare.com

BoironUSA.com

Info@Boiron.com

1-800-BOIRON-1

(1-800-264-7661)

Distributed by Boiron Inc.

Newtown Square, PA 19073

do not use if glued carton end flaps are open

dispose of 1 year after opening

0.5 oz (14 g)

1.4 oz (40 g)

2.5 oz (70 g)

4.2 oz (120 g)

Pain Relief*

Muscle Pain & Stiffness Swelling from Injuries Bruises*

*CLAIMS BASED ON TRADITIONAL HOMEOPATHIC PRACTICE NOT ACCEPTED MEDICAL EVIDENCE. NOT FDA EVALUATED.
**C,K,CK, and X are homeopathic dilutions: see BoironUSA.com/info for details.

The letters "HPUS" indicate that the components in this product are officially monographed in the Homeopathic Pharmacopoeia of the United States.

ɨ Homeopathic mother tincture made from Arnica montana fresh whole plant.